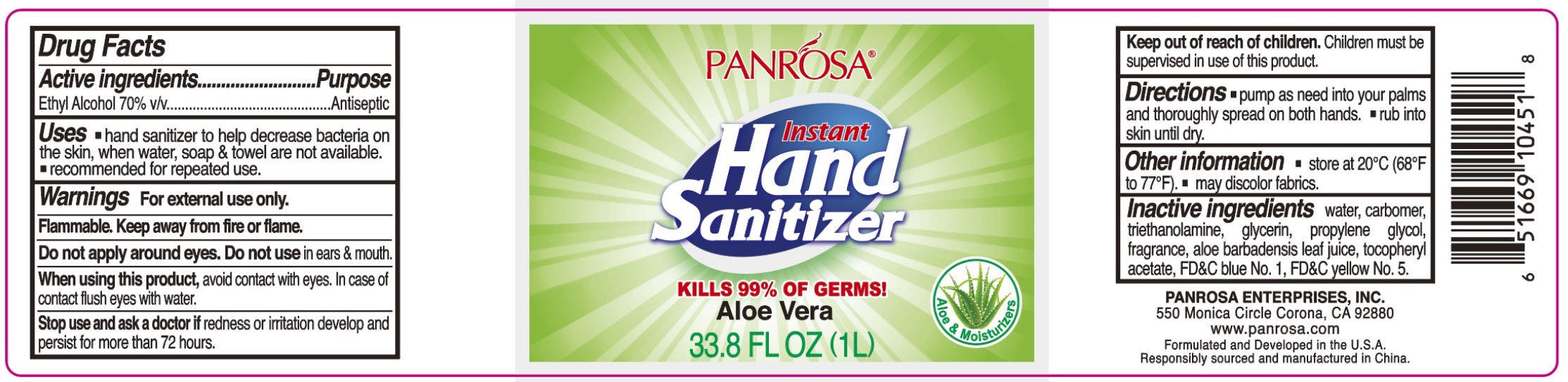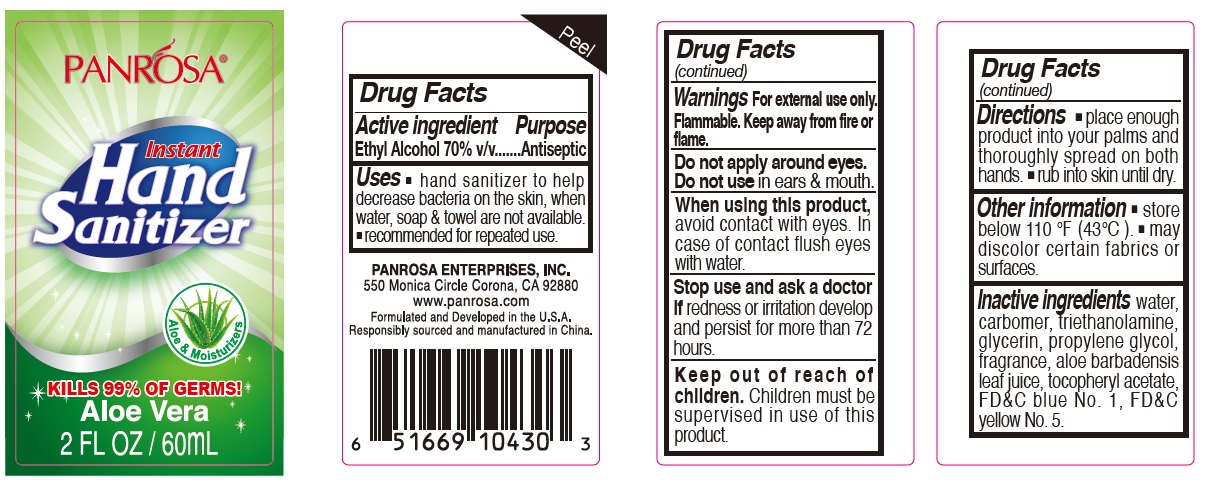 DRUG LABEL: Panrosa Instant Hand Sanitizer Aloe Vera
NDC: 50302-013 | Form: GEL
Manufacturer: Panrosa Enterprises, Inc.
Category: otc | Type: HUMAN OTC DRUG LABEL
Date: 20211020

ACTIVE INGREDIENTS: ALCOHOL 0.7 mL/1 mL
INACTIVE INGREDIENTS: WATER; CARBOMER HOMOPOLYMER, UNSPECIFIED TYPE; TROLAMINE; GLYCERIN; PROPYLENE GLYCOL; ALOE VERA LEAF; .ALPHA.-TOCOPHEROL ACETATE; FD&C BLUE NO. 1; FD&C YELLOW NO. 5

Panrosa Instant Hand Sanitizer Aloe Vera

Active ingredient

Ethyl Alcohol 70% v/v

Purpose

Antiseptic

Uses

- hand sanitizer to help decrease bacteria on the skin, when water, soap & towel are not available.
- recommended for repeated use.

Warnings

For external use only. Flammable. Keep away from fire or flame.

Do not apply around eyes.

Do not use

in ears & mouth.

When using this product,

avoid contact with eyes. In case of contact flush eyes with water.

Stop use and ask a doctor if

redness or irritation develop and persist for more than 72 hours.

Keep out of reach of children.

Children must be supervised in use of this product.

Directions

- place enough product into your palms and thoroughly spread on both hands.
- rub into skin until dry.

Other information

- store below 110 ℉ (43℃).
- may discolor certain fabrics or surfaces.

Inactive ingredients

water, carbomer, triethanolamine, glycerin, propylene glycol, fragrance, aloe barbadensis leaf juice, tocopheryl acetate, FD&C blue No. 1, FD&C yellow No. 5.